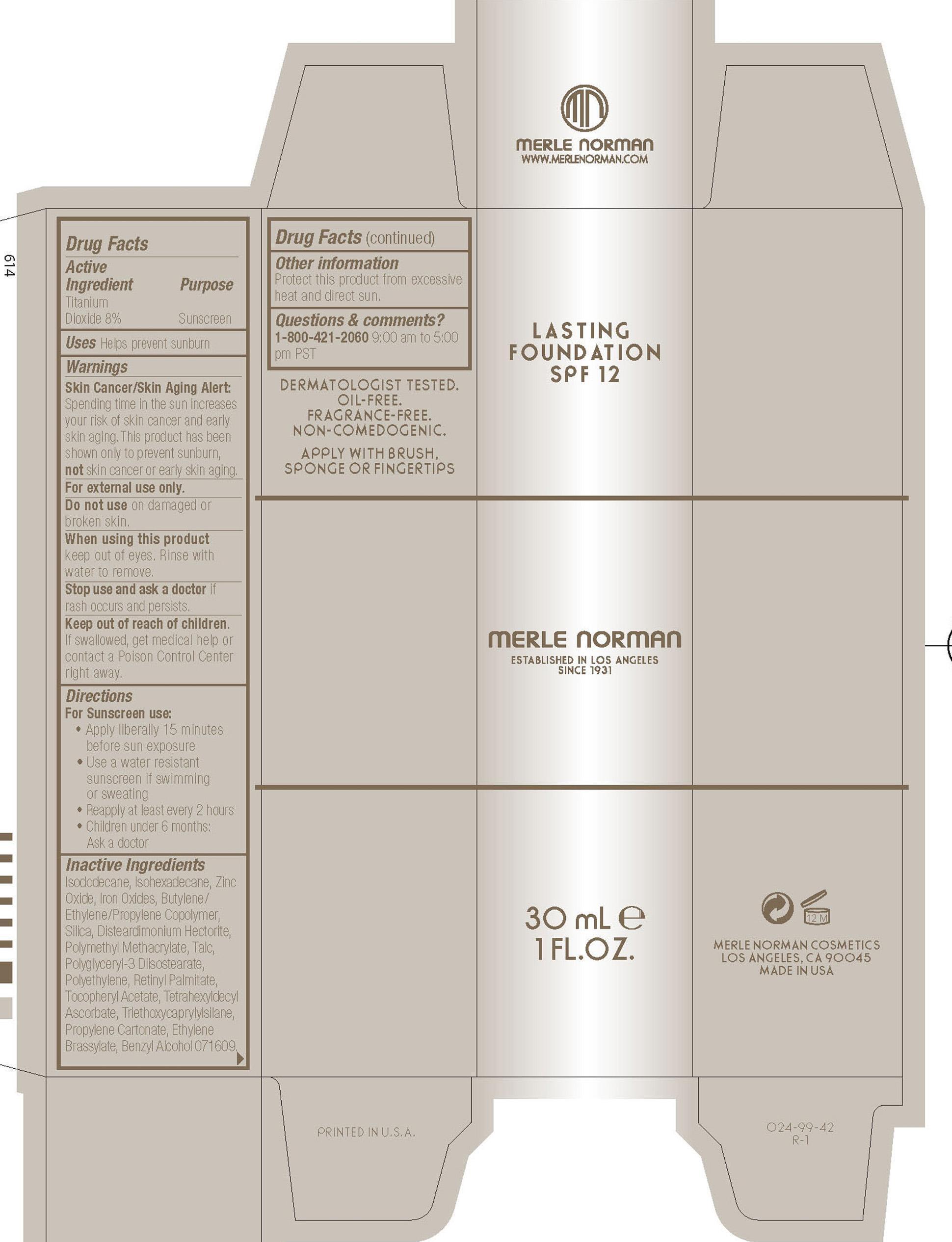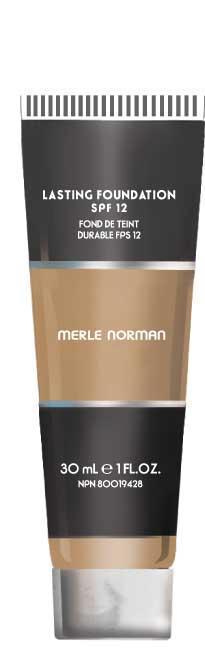 DRUG LABEL: Lasting Foundation SPF 12
NDC: 57627-110 | Form: CREAM
Manufacturer: Merle Norman Cosmetics, Inc
Category: otc | Type: HUMAN OTC DRUG LABEL
Date: 20251119

ACTIVE INGREDIENTS: TITANIUM DIOXIDE 2.4 g/30 g
INACTIVE INGREDIENTS: ISODODECANE; ISOHEXADECANE; ZINC OXIDE; FERROUS OXIDE; FERRIC OXIDE RED; FERRIC OXIDE YELLOW; FERROSOFERRIC OXIDE; SILICON DIOXIDE; TALC; VITAMIN A PALMITATE; TETRAHEXYLDECYL ASCORBATE; PROPYLENE CARBONATE; ETHYLENE BRASSYLATE; BENZYL ALCOHOL

Merle Norman Lasting Foundation SPF 12

active ingredients Purpose

Titanium Dioxide 8% Sunscreen

Uses
· helps prevent sunburn

· Keep out of reach of children. If product is swallowed, get medical help or
contact a Poison Control Center right away.

· Stop use and ask a doctor if rash occurs and persists

WARNINGS
Skin Cancer/Skin Aging Alert: Spending time in the sun increases your risk of skin cancer and early skin aging. This product has been shown only to help prevent sunburn, not skin cancer or early skin aging.
For external use only
Do not use on damaged or broken skin
When using this product keep out of eyes. Rinse with water to remove.

Directions

For Sunscreen use
· Apply liberally 15 minutes before sun exposure
· Reapply at least every 2 hours
· Use a water resistant sunscreen if swimming or sweating
· Children under 6 months of age: Ask a doctor

INACTIVE INGREDIENT

ISODODECANE,ISOHEXADECANE, ZINC OXIDE (CI 77947), IRON OXIDES ,BUTYLENE/ETHYLENE/PROPYLENE COPOLYMER , SILICA ,DISTEARDIMONIUM HECTORITE, POLYMETHYL METHACRYLATE,TALC,POLYGLYCERYL - 3 DIISOSTEARATE ,
POLYETHYLENE, RETINYL PALMITATE, TOCOPHERYL ACETATE, TETRAHEXYLDECYL ASCORBATE , TRI ETHOXYCAPRYLYLSILANE , PROPYLENE CARBONATE, ETHYLEN E B RASSYLATE, BENZYL ALCOHOL

PACKAGE LABEL

Lasting Foundation
SPF 12
Fond De Teint
Durable FPS 12

Merle Norman

30 mL 1 FL. OZ.